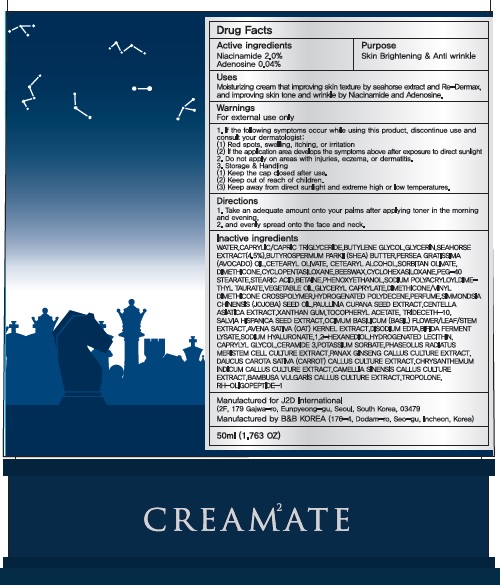 DRUG LABEL: CRE AM2ATE Knight Seahorse
NDC: 69958-130 | Form: CREAM
Manufacturer: J2D INTERNATIONAL
Category: otc | Type: HUMAN OTC DRUG LABEL
Date: 20170927

ACTIVE INGREDIENTS: Niacinamide 1.0 g/50 mL; Adenosine 0.02 g/50 mL
INACTIVE INGREDIENTS: WATER; BUTYLENE GLYCOL

ACTIVE INGREDIENT

Active ingredients: Niacinamide 2.0%, Adenosine 0.04%

INACTIVE INGREDIENT

Inactive ingredients: WATER,CAPRYLIC/CAPRIC TRIGLYCERIDE,BUTYLENE GLYCOL,GLYCERIN,SEAHORSE EXTRACT(4.5%),BUTYROSPERMUM PARKII (SHEA) BUTTER,PERSEA GRATISSIMA (AVOCADO) OIL,CETEARYL OLIVATE, CETEARYL ALCOHOL,SORBITAN OLIVATE,DIMETHICONE,CYCLOPENTASILOXANE,BEESWAX,CYCLOHEXASILOXANE,PEG-40 STEARATE,STEARIC ACID,BETAINE,PHENOXYETHANOL,SODIUM POLYACRYLOYLDIMETHYL TAURATE,VEGETABLE OIL,GLYCERYL CAPRYLATE,DIMETHICONE/VINYL DIMETHICONE CROSSPOLYMER,HYDROGENATED POLYDECENE,PERFUME,SIMMONDSIA CHINENSIS (JOJOBA) SEED OIL,PAULLINIA CUPANA SEED EXTRACT,CENTELLA ASIATICA EXTRACT,XANTHAN GUM,TOCOPHERYL ACETATE, TRIDECETH-10,SALVIA HISPANICA SEED EXTRACT,OCIMUM BASILICUM (BASIL) FLOWER/LEAF/STEM EXTRACT,AVENA SATIVA (OAT) KERNEL EXTRACT,DISODIUM EDTA,BIFIDA FERMENT LYSATE,SODIUM HYALURONATE,1,2-HEXANEDIOL,HYDROGENATED LECITHIN,CAPRYLYL GLYCOL,CERAMIDE 3,POTASSIUM SORBATE,PHASEOLUS RADIATUS MERISTEM CELL CULTURE EXTRACT,PANAX GINSENG CALLUS CULTURE EXTRACT,DAUCUS CAROTA SATIVA (CARROT) CALLUS CULTURE EXTRACT,CHRYSANTHEMUM INDICUM CALLUS CULTURE EXTRACT,CAMELLIA SINENSIS CALLUS CULTURE EXTRACT,BAMBUSA VULGARIS CALLUS CULTURE EXTRACT,TROPOLONE,RH-OLIGOPEPTIDE-1

PURPOSE

Purpose: Skin Brightening & Anti wrinkle

WARNINGS

Warnings: For external use only

1. If the following symptoms occur while using this product, discontinue use and consult your dermatologist: (1) Red spots, swelling, itching, or irritation (2) If the application area develops the symptoms above after exposure to direct sunlight

2. Do not apply on areas with injuries, eczema, or dermatitis.

3. Storage & Handling (1) Keep the cap closed after use. (2) Keep out of reach of children. (3) Keep away from direct sunlight and extreme high or low temperatures.

KEEP OUT OF REACH OF CHILDREN

Uses

Uses: Moisturizing cream that improving skin texture by seahorse extract and Re-Dermax, and improving skin tone and wrinkle by Niacinamide and Adenosine.

Directions

Directions: 1.Take an adequate amount onto your palms after applying toner in the morning and evening, 2.and evenly spread onto the face and neck.